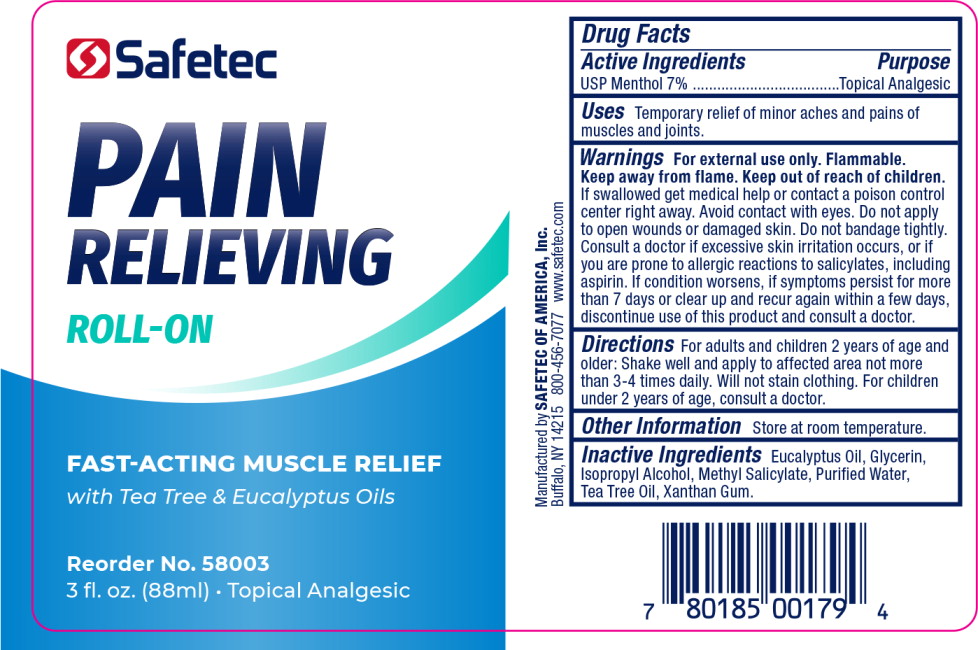 DRUG LABEL: Pain Relieving Roll-On
NDC: 61010-1550 | Form: GEL
Manufacturer: Safetec of America, Inc.
Category: otc | Type: HUMAN OTC DRUG LABEL
Date: 20240205

ACTIVE INGREDIENTS: MENTHOL, UNSPECIFIED FORM 7 g/100 mL
INACTIVE INGREDIENTS: EUCALYPTUS OIL; GLYCERIN; ISOPROPYL ALCOHOL; METHYL SALICYLATE; WATER; TEA TREE OIL; XANTHAN GUM

61010-1550-1, Pain Relieving Roll-on

Drug Facts

Active Ingredients

USP Menthol 7%

Purpose

Topical Analgesic

Uses

Temporary relief of minor aches and pains of muscles and joints.

Warnings

For external use only. Flammable.

Keep away from flame. Keep out of reach of children.

If swallowed get medical help or contact a poison control center right away. Avoid contact with eyes. Do not apply to open wounds or damaged skin. Do not bandage tightly.

Consult a doctor if excessive skin irritation occurs, or if you are prone to allergic reactions to salicylates, including aspirin. If condition worsens, if symptoms persist for more than 7 days or clear up and recur again within a few days, discontinue use of this product and consult a doctor.

Directions

For adults and children 2 years of age and older: Shake well and apply to affected area not more than 3-4 times daily. Will not stain clothing. For children under 2 years of age, consult a doctor.

Other Information

Store at room temperature.

Inactive Ingredients

Eucalyptus Oil, Glycerin, Isopropyl Alcohol, Methyl Salicylate, Purified Water, Tea Tree Oil, Xanthan Gum.

Principal Display Panel - 3 oz. Bottle Label

Safetec

PAIN RELIEVING

ROLL-ON

FAST-ACTING MUSCLE RELIEF

with Tea Tree & Eucalyptus Oils

Reorder No. 58003

3 fl. oz. (88ml) • Topical Analgesic